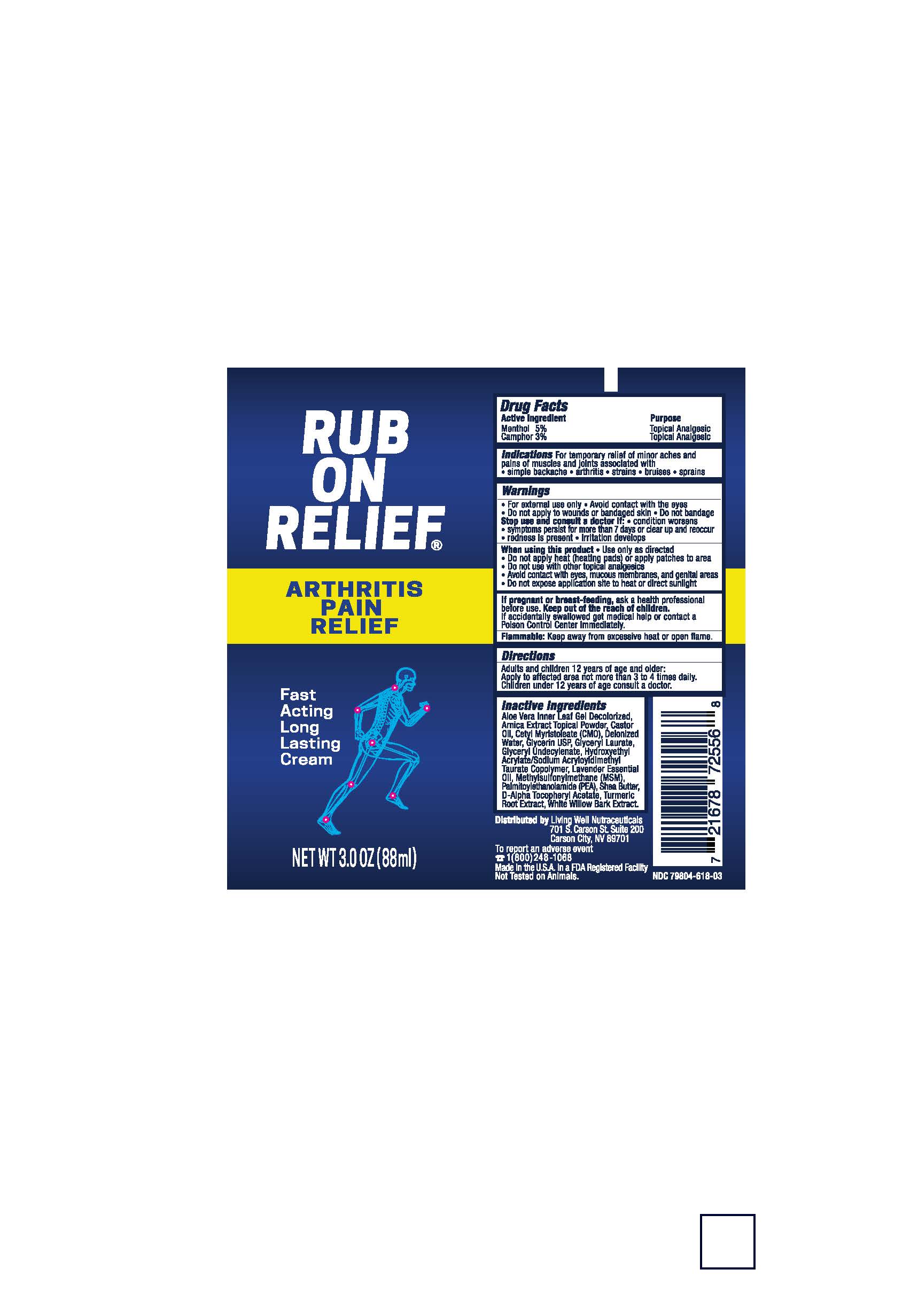 DRUG LABEL: Healthy Back Institute Rub On Relief
NDC: 79804-618 | Form: CREAM
Manufacturer: Eagle Labs Inc.
Category: otc | Type: HUMAN OTC DRUG LABEL
Date: 20260121

ACTIVE INGREDIENTS: MENTHOL 0.05 g/1 g; CAMPHOR (SYNTHETIC) 0.03 g/1 g
INACTIVE INGREDIENTS: ALOE VERA LEAF; ARNICA MONTANA FLOWER; CASTOR OIL; CETYL MYRISTOLEATE; WATER; GLYCERIN; GLYCERYL LAURATE; GLYCERYL RICINOLEATE; HYDROXYETHYL ACRYLATE/SODIUM ACRYLOYLDIMETHYL TAURATE COPOLYMER (45000 MPA.S AT 1%); LAVENDER OIL; DEMETON-S-METHYLSULFONE; 1-PALMITOYL-2-OLEOYL-SN-GLYCERO-3-(PHOSPHO-RAC-(1-GLYCEROL)); SHEA BUTTER; WILLOW BARK; DISODIUM .ALPHA.-TOCOPHERYL PHOSPHATE, D-; TURMERIC

Pain Cream

Active Ingredient

Menthol 5%

Camphor 3%

Purpose

Topical Analgesic

Uses:

For Temporary relief of minor aches and pains of muscles and joints associated with simple backache, arthritis, strains, bruises, and sprains.

WARNINGS:

For external use only ▪Avoid contact with the eyes ▪ Do not apply to wounds or bandaged skin ▪ Do not bandage

Stop use and consult a doctor if: ▪ condition worsens ▪ symptoms persist for more than 7 days or clear up and reoccur ▪redness is present ▪irritation develops

Keep out of reach of children

Keep out of the reach of children.
If accidentally swallowed get medical help or contact a Poison Control Center immediately.

If pregnant or breast-feeding, ask a health professional before use. Keep out of the reach of children. If accidentally swallowed, get medical help or contact a Poison Control Center immediately

Stop Usage immediately and as a doctor if:

The condition worsens or symptoms persist for more than 7 days or clear up and reoccur, redness or swelling is present, irritation develops

When using this product ▪ use only as directed ▪ do not apply heat (heating pads) or apply patches to area ▪ do not use with other topical analgesics - avoid contact with eyes, mucos membranes, and genital area - Do not expose application site to heat or direct sunlight

Other Information

Flammable: Keep away from excessive heat or open flame. Keep out of direct sunlight: Store at 50-86F (15-30C)

Directions:

Adults and children 12 years of age and older: Apply to the affected area not more than 3 to 4 times daily. Children under 12 years of age consult a doctor.

Inactive Ingredients:

Aloe Barbadensis Inner Leaf Juice, Aqua, Arnica Montana Flower Extract, Ricinus Communis (Castor) Seed Oil, Cetyl Myristoleate, Glycerin USP, Caprylyl Glycol, Glyceryl Laurate, Glyceryl Undecylenate, Hydroxyethyl Acrylate/Sodium Acryloyldimethyl Taurate Copolymer, Lavandula Angustifolia (Lavender) Oil, Methyl Sulfonyl Methane, Palmitoylethanolamide, Butyrospermum Parkii (Shea) Butter, D-Alpha Tocopheryl Acetate, Curcuma Longa (Turmeric) Root Extract, Salix Alba (Willow) Bark Extract.

RUB THE PAIN AWAY

Rub On Relief Net Wt 3.0 OZ (88mL)